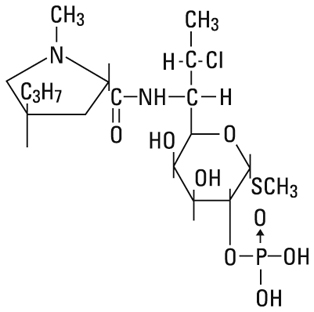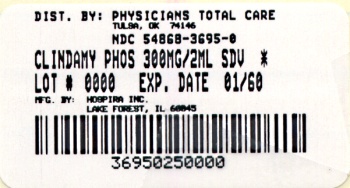 DRUG LABEL: Clindamycin Phosphate
NDC: 54868-3695 | Form: INJECTION, SOLUTION
Manufacturer: Physicians Total Care, Inc.
Category: prescription | Type: HUMAN PRESCRIPTION DRUG LABEL
Date: 20101018

ACTIVE INGREDIENTS: CLINDAMYCIN PHOSPHATE 150 mg/1 mL
INACTIVE INGREDIENTS: EDETATE DISODIUM 0.5 mg/1 mL; BENZYL ALCOHOL 9.45 mg/1 mL; SODIUM HYDROXIDE; HYDROCHLORIC ACID

Fliptop Vial

Rx only

To reduce the development of drug-resistant bacteria and maintain the effectiveness of clindamycin and other antibacterial drugs, clindamycin should be used only to treat or prevent infections that are proven or strongly suspected to be caused by bacteria.

WARNING

Clostridium difficile associated diarrhea (CDAD) has been reported with use of nearly all antibacterial agents, including clindamycin, and may range in severity from mild diarrhea to fatal colitis. Treatment with antibacterial agents alters the normal flora of the colon leading to overgrowth of C. difficile.

Because clindamycin therapy has been associated with severe colitis which may end fatally, it should be reserved for serious infections where less toxic antimicrobial agents are inappropriate, as described in the INDICATIONS AND USAGE section. It should not be used in patients with nonbacterial infections such as most upper respiratory tract infections. C. difficile produces toxins A and B which contribute to the development of CDAD. Hypertoxin producing strains of C. difficile cause increased morbidity and mortality, as these infections can be refractory to antimicrobial therapy and may require colectomy. CDAD must be considered in all patients who present with diarrhea following antibiotic use. Careful medical history is necessary since CDAD has been reported to occur over two months after the administration of antibacterial agents.

If CDAD is suspected or confirmed, ongoing antibiotic use not directed against C. difficile may need to be discontinued. Appropriate fluid and electrolyte management, protein supplementation, antibiotic treatment of C. difficile, and surgical evaluation should be instituted as clinically indicated.

DESCRIPTION

Clindamycin Injection, USP, a water soluble ester of clindamycin and phosphoric acid, is a sterile solution for intramuscular or intravenous use.

May contain sodium hydroxide and/or hydrochloric acid for pH adjustment. pH is 6.5 range 5.5 to 7.0.

Clindamycin is a semisynthetic antibiotic produced by a 7(S)-chloro-substitution of the 7 (R)-hydroxyl group of the parent compound lincomycin.

The chemical name of clindamycin phosphate is methyl 7-chloro-6,7,8-trideoxy-6-(1-methyl-trans-4-propyl-L-2-pyrrolidinecarboxamido)-1-thio-L-threo-α-D-galacto-octopyranoside 2-(dihydrogen phosphate).

The molecular formula is C18H34ClN2O8PS and the molecular weight is 504.97.

The structural formula is represented below:

Each mL contains clindamycin phosphate equivalent to 150 mg clindamycin, 0.5 mg disodium edetate and 9.45 mg benzyl alcohol added as a preservative.

CLINICAL PHARMACOLOGY

Biologically inactive clindamycin phosphate is rapidly converted to active clindamycin.

By the end of short-term intravenous infusion, peak serum levels of active clindamycin are reached. Biologically inactive clindamycin phosphate disappears rapidly from the serum; the average elimination half-life is 6 minutes; however, the serum elimination half-life of active clindamycin is about 3 hours in adults and 2½ hours in pediatric patients.

After intramuscular injection of clindamycin phosphate, peak levels of active clindamycin are reached within 3 hours in adults and 1 hour in pediatric patients. Serum level curves may be constructed from I.V. peak serum levels as given in Table 1 by application of elimination half-lives listed above.

Serum levels of clindamycin can be maintained above the in vitro minimum inhibitory concentrations for most indicated organisms by administration of clindamycin phosphate every 8 to 12 hours in adults and every 6 to 8 hours in pediatric patients, or by continuous intravenous infusion. An equilibrium state is reached by the third dose.

The elimination half-life of clindamycin is increased slightly in patients with markedly reduced renal or hepatic function. Hemodialysis and peritoneal dialysis are not effective in removing clindamycin from the serum. Dosage schedules need not be modified in the presence of mild or moderate renal or hepatic disease.

No significant levels of clindamycin are attained in the cerebrospinal fluid, even in the presence of inflamed meninges.

Pharmacokinetic studies in elderly volunteers (61 to 79 years) and younger adults (18 to 39 years) indicate that age alone does not alter clindamycin pharmacokinetics (clearance, elimination half-life, volume of distribution, and area under the serum concentration-time curve) after I.V. administration of clindamycin phosphate. After oral administration of clindamycin hydrochloride, elimination half-life is increased to approximately 4 hours (range 3.4 to 5.1 h) in the elderly compared to 3.2 hours (range 2.1 to 4.2 h) in younger adults. The extent of absorption, however, is not different between the age groups and no dosage alteration is necessary for the elderly with normal hepatic function and normal (age-adjusted) renal function^1.

Serum assays for active clindamycin require an inhibitor to prevent in vitro hydrolysis of clindamycin phosphate.

Table 1 Average Peak and Trough Serum Concentrations of Active Clindamycin After Dosing with Clindamycin Phosphate
Dosage Regimen | Peak; mcg/mL | Trough; mcg/mL
Healthy Adult Males (Post equilibrium)
600 mg I.V. in 30 min q6h; 600 mg I.V. in 30 min q8h; 900 mg I.V. in 30 min q8h; 600 mg I.M. q12* | 10.9; 10.8; 14.1; 9 | 2; 1.1; 1.7
Pediatric Patients (first dose)*
5-7 mg/kg I.V. in 1 hour; 5-7 mg/kg I.M.; 3-5 mg/kg I.M. | 10; 8; 4

*Data in this group from patients being treated for infection.

Microbiology: Although clindamycin phosphate is inactive in vitro, rapid in vivo hydrolysis converts this compound to the antibacterially active clindamycin.

Clindamycin has been shown to have in vitro activity against isolates of the following organisms:

Aerobic gram positive cocci,including:

Staphylococcus aureus (penicillinase and non-penicillinase producing strains). When tested by in vitro methods, some staphylococcal strains

originally resistant to erythromycin rapidly develop resistance to clindamycin.

Staphylococcus epidermidis (penicillinase and non-penicillinase producing strains). When tested by in vitro methods, some staphylococcal strains

originally resistant to erythromycin rapidly develop resistance to clindamycin.

Streptococci (exceptEnterococcus faecalis)

Pneumococci

Anaerobic gram negative bacilli,including:

Bacteroides species (including Bacteroides fragilis group and Bacteroides melaninogenicus group)

Fusobacterium species

Anaerobic gram positive nonsporeforming bacilli, including:

Propionibacterium

Eubacterium

Actinomyces species

Anaerobic and microaerophilic gram positive cocci, including:

Peptococcus species

Peptostreptococcus species

Microaerophilic streptococci

Clostridia: Clostridia are more resistant than most anaerobes to clindamycin. Most Clostridium perfringens are susceptible, but other species, e.g.,

Clostridium sporogenes and Clostridium tertium are frequently resistant to clindamycin. Susceptibility testing should be done.

Cross resistance has been demonstrated between clindamycin and lincomycin.

Antagonism has been demonstrated betweeen clindamycin and erythromycin.

In vitro Susceptibility Testing:

Disk diffusion technique-Quantitative methods that require measurement of zone diameters give the most precise estimates of antibiotic susceptibility. One such procedure^2 has been recommended for use with disks to test susceptibility to clindamycin.

Reports from a laboratory using the standardized single-disk susceptibility test^1 with a 2 mcg clindamycin disk should be interpreted according to the following criteria:

Susceptible organisms produce zones of 17 mm or greater, indicating that the tested organism is likely to respond to therapy.

Organisms of intermediate susceptibility produce zones of 15-16 mm, indicating that the tested organism would be susceptible if a high dosage is used or if the infection is confined to tissues and fluids (e.g., urine), in which high antibiotic levels are attained.

Resistant organisms produce zones of 14 mm or less, indicating that other therapy should be selected.

Standardized procedures require the use of control organisms. The 2 mcg clindamycin disk should give a zone diameter between 24 and 30 mm for S. aureus ATCC 25923.

Dilution techniques − A bacterial isolate may be considered susceptible if the minimum inhibitory concentration (MIC) for clindamycin is not more than 1.6 mcg/mL. Organisms are considered moderately susceptible if the MIC is greater than 1.6 mcg/mL and less than or equal to 4.8 mcg/mL. Organisms are considered resistant if the MIC is greater than 4.8 mcg per mL. The range of MIC’s for the control strains are as follows:

S. aureus ATCC 29213, 0.06 to 0.25 mcg/mL.

E. faecalis ATCC 29212, 4 to 16 mcg/mL.

For anaerobic bacteria the minimum inhibitory concentration (MIC) of clindamycin can be determined by agar dilution and broth dilution (including microdilution) techniques.^3 If MICs are not determined routinely, the disk broth method is recommended for routine use. The KIRBY-BAUER DISK DIFFUSION METHOD AND ITS INTERPRETIVE STANDARDS ARE NOT RECOMMENDED FOR ANAEROBES.

INDICATIONS AND USAGE

Clindamycin Injection, USP is indicated in the treatment of serious infections caused by susceptible anaerobic bacteria.

Clindamycin Injection, USP is also indicated in the treatment of serious infections due to susceptible strains of streptococci, pneumococci, and staphylococci. Its use should be reserved for penicillin-allergic patients or other patients for whom, in the judgment of the physician, a penicillin is inappropriate. Because of the risk of antibiotic-associated pseudomembranous colitis, as described in the WARNING box, before selecting clindamycin the physician should consider the nature of the infection and the suitability of less toxic alternatives (e.g., erythromycin).

Bacteriologic studies should be performed to determine the causative organisms and their susceptibility to clindamycin.

Indicated surgical procedures should be performed in conjunction with antibiotic therapy.

Clindamycin Injection, USP is indicated in the treatment of serious infections caused by susceptible strains of the designated organisms in the conditions listed below:

Lower respiratory tract infections including pneumonia, empyema, and lung abscess caused by anaerobes, Streptococcus pneumoniae, other streptococci (except E. faecalis), and Staphylococcus aureus.

Skin and skin structure infections caused by Streptococcus pyogenes, Staphylococcus aureus, and anaerobes.

Gynecological infections including endometritis, nongonococcal tubo-ovarian abscess, pelvic cellulitis, and postsurgical vaginal cuff infection caused by susceptible anaerobes.

Intra-abdominal infections including peritonitis and intra-abdominal abscess caused by susceptible anaerobic organisms.

Septicemia caused by Staphylococcus aureus, streptococci (except Enterococcus faecalis), and susceptible anaerobes.

Bone and joint infections including acute hematogenous osteomyelitis caused by Staphylococcus aureus and as adjunctive therapy in the surgical treatment of chronic bone and joint infections due to susceptible organisms.

To reduce the development of drug-resistant bacteria and maintain the effectiveness of clindamycin and other antibacterial drugs, clindamycin should be used only to treat or prevent infections that are proven or strongly suspected to be caused by susceptible bacteria. When culture and susceptibility information are available, they should be considered in selecting or modifying antibacterial therapy. In the absence of such data, local epidemiology and susceptibility patterns may contribute to the empiric selection of therapy.

CONTRAINDICATIONS

This drug is contraindicated in individuals with a history of hypersensitivity to preparations containing clindamycin or lincomycin.

WARNINGS

See WARNING box.

Clostridium difficile associated diarrhea (CDAD) has been reported with use of nearly all antibacterial agents, including clindamycin, and may range in severity from mild diarrhea to fatal colitis. Treatment with antibacterial agents alters the normal flora of the colon leading to overgrowth of C. difficile.

C. difficile produces toxins A and B which contribute to the development of CDAD. Hypertoxin producing strains of C. difficile cause increased morbidity and mortality, as these infections can be refractory to antimicrobial therapy and may require colectomy. CDAD must be considered in all patients who present with diarrhea following antibiotic use. Careful medical history is necessary since CDAD has been reported to occur over two months after the administration of antibacterial agents.

If CDAD is suspected or confirmed, ongoing antibiotic use not directed against C. difficile may need to be discontinued. Appropriate fluid and electrolyte management, protein supplementation, antibiotic treatment of C. difficile, and surgical evaluation should be instituted as clinically indicated.

A careful inquiry should be made concerning previous sensitivities to drugs and other allergens.

This product contains benzyl alcohol as a preservative. Benzyl alcohol has been associated with a fatal “Gasping Syndrome” in premature infants. (See PRECAUTIONS− Pediatric Use).

Usage in Meningitis: Since clindamycin does not diffuse adequately into the cerebrospinal fluid, the drug should not be used in the treatment of meningitis.

SERIOUS ANAPHYLACTOID REACTIONS REQUIRE IMMEDIATE EMERGENCY TREATMENT WITH EPINEPHRINE. OXYGEN AND INTRAVENOUS CORTICOSTEROIDS SHOULD ALSO BE ADMINISTERED AS INDICATED.

PRECAUTIONS

General

Review of experience to date suggests that a subgroup of older patients with associated severe illness may tolerate diarrhea less well. When clindamycin is indicated in these patients, they should be carefully monitored for change in bowel frequency.

Clindamycin phosphate should be prescribed with caution in individuals with a history of gastrointestinal disease, particularly colitis.

Clindamycin phosphate should be prescribed with caution in atopic individuals.

Certain infections may require incision and drainage or other indicated surgical procedures in addition to antibiotic therapy.

The use of clindamycin phosphate may result in overgrowth of nonsusceptible organisms− particularly yeasts. Should superinfections occur, appropriate measures should be taken as indicated by the clinical situation.

Clindamycin phosphate should not be injected intravenously undiluted as a bolus, but should be infused over at least 10-60 minutes as directed in the DOSAGE AND ADMINISTRATION section.

Clindamycin dosage modification may not be necessary in patients with renal disease. In patients with moderate to severe liver disease, prolongation of clindamycin half-life has been found. However, it was postulated from studies that when given every eight hours, accumulation should rarely occur. Therefore, dosage modification in patients with liver disease may not be necessary. However, periodic liver enzyme determinations should be made when treating patients with severe liver disease.

Prescribing clindamycin in the absence of a proven or strongly suspected bacterial infection or a prophylactic indication is unlikely to provide benefit to the patient and increases the risk of the development of drug-resistant bacteria.

Information for Patients

Patients should be counseled that antibacterial drugs including clindamycin should only be used to treat bacterial infections. They do not treat viral infections (e.g., the common cold). When clindamycin is prescribed to treat a bacterial infection, patients should be told that although it is common to feel better early in the course of therapy, the medication should be taken exactly as directed. Skipping doses or not completing the full course of therapy may (1) decrease the effectiveness of the immediate treatment and (2) increase the likelihood that bacteria will develop resistance and will not be treatable by clindamycin or other antibacterial drugs in the future.

Diarrhea is a common problem caused by antibiotics which usually ends when the antibiotic is discontinued. Sometimes after starting treatment with antibiotics, patients can develop watery and bloody stools (with or without stomach cramps and fever) even as late as two or more months after having taken the last dose of the antibiotic. If this occurs, patients should contact their physician as soon as possible.

Laboratory Tests

During prolonged therapy periodic liver and kidney function tests and blood counts should be performed.

Drug Interactions

Clindamycin has been shown to have neuromuscular blocking properties that may enhance the action of other neuromuscular blocking agents. Therefore, it should be used with caution in patients receiving such agents.

Antagonism has been demonstrated between clindamycin and erythromycin in vitro. Because of possible clinical significance, the two drugs should not be administered concurrently.

Carcinogenesis, Mutagenesis, Impairment of Fertility

Long term studies in animals have not been performed with clindamycin to evaluate carcinogenic potential. Genotoxicity tests performed included a rat micronucleus test and an Ames Salmonella reversion test. Both tests were negative.

Fertility studies in rats treated orally with up to 300 mg/kg/day (approximately 1.1 times the highest recommended adult human dose based on mg/m^2) revealed no effects on fertility or mating ability.

Pregnancy:

Teratogenic Effects: Pregnancy Category B

Reproduction studies performed in rats and mice using oral doses of clindamycin up to 600 mg/kg/day (2.1 and 1.1 times the highest recommended adult human dose based on mg/m^2, respectively) or subcutaneous doses of clindamycin up to 250 mg/kg/day (0.9 and 0.5 times the highest recommended adult human dose based on mg/m^2, respectively) revealed no evidence of teratogenicity.

There are, however, no adequate and well-controlled studies in pregnant women. Because animal reproduction studies are not always predictive of the human response, this drug should be used during pregnancy only if it is clearly needed.

Nursing Mothers

Clindamycin has been reported to appear in breast milk in the range of 0.7 to 3.8 mcg/mL at dosages of 150 mg orally to 600 mg intravenously. Because of the potential for adverse reactions due to clindamycin in neonates (see Pediatric Use), the decision to discontinue the drug should be made, taking into account the importance of the drug to the mother.

Pediatric Use

When clindamycin phosphate injection is administered to the pediatric population (birth to 16 years) appropriate monitoring of organ system functions is desirable.

Usage in Newborns and Infants

This product contains benzyl alcohol as a preservative. Benzyl alcohol has been associated with a fatal “Gasping Syndrome” in premature infants.

The potential for the toxic effect in the pediatric population from chemicals that may leach from the single dose premixed IV preparation in plastic has not been evaluated.

Geriatric Use

Clinical studies of clindamycin did not include sufficient numbers of patients age 65 and over to determine whether they respond differently from younger patients. However, other reported clinical experience indicates that antibiotic-associated colitis and diarrhea (due to Clostridium difficile) seen in association with most antibiotics occur more frequently in the elderly (>60 years) and may be more severe. These patients should be carefully monitored for the development of diarrhea.

Pharmacokinetic studies with clindamycin have shown no clinically important differences between young and elderly subjects with normal hepatic function and normal (age-adjusted) renal function after oral or intravenous administration.

ADVERSE REACTIONS

The following reactions have been reported with the use of clindamycin.

Gastrointestinal: Antibiotic-associated colitis (see WARNINGS), pseudomembranous colitis abdominal pain, nausea and vomiting. The onset of pseudomembranous colitis symptoms may occur during or after antibacterial treatment (see WARNINGS). An unpleasant or metallic taste occasionally has been reported after intravenous administration of the higher doses of clindamycin phosphate.

Hypersensitivity Reactions: Maculopapular rash and urticaria have been observed during drug therapy. Generalized mild to moderate morbilliform-like skin rashes are the most frequently reported of all adverse reactions. Rare instances of erythema multiforme, some resembling Stevens-Johnson syndrome, have been associated with clindamycin. A few cases of anaphylactoid reactions have been reported. If a hypersensitivity reaction occurs, the drug should be discontinued. The usual agents (epinephrine, corticosteroids, antihistamines) should be available for emergency treatment of serious reactions.

Skin and Mucous Membranes: Pruritus, vaginitis, and rare instances of exfoliative dermatitis have been reported. (See Hypersensitivity Reactions).

Liver: Jaundice and abnormalities in liver function tests have been observed during clindamycin therapy.

Renal: Although no direct relationship of clindamycin to renal damage has been established, renal dysfunction as evidenced by azotemia, oliguria, and/or proteinuria has been observed in rare instances.

Hematopoietic: Transient neutropenia (leukopenia) and eosinophilia have been reported. Reports of agranulocytosis and thrombocytopenia have been made. No direct etiologic relationship to concurrent clindamycin therapy could be made in any of the foregoing.

Local Reactions: Pain, induration and sterile abscess have been reported after intramuscular injection and thrombophlebitis after intravenous infusion. Reactions can be minimized or avoided by giving deep intramuscular injections and avoiding prolonged use of indwelling intravenous catheters.

Musculoskeletal: Rare instances of polyarthritis have been reported.

Cardiovascular: Rare instances of cardiopulmonary arrest and hypotension have been reported following too rapid intravenous administration. (See DOSAGE AND ADMINISTRATION).

OVERDOSAGE

Significant mortality was observed in mice at an intravenous dose of 855 mg/kg and in rats at an oral or subcutaneous dose of approximately 2618 mg/kg. In the mice, convulsions and depression were observed.

Hemodialysis and peritoneal dialysis are not effective in removing clindamycin from the serum.

DOSAGE AND ADMINISTRATION

If diarrhea occurs during therapy, this antibiotic should be discontinued. (See WARNING box).

Adults:

Parenteral (I.M. or I.V. Administration):

Serious infections due to aerobic gram-positive cocci and the more susceptible anaerobes (NOT generally including Bacteroides fragilis, Peptococcus species and Clostridium species other than Clostridium perfringens):

600 to 1200 mg/day in 2, 3 or 4 equal doses.

More severe infections, particularly those due to proven or suspected Bacteroides fragilis, Peptococcus species, or Clostridium species other than Clostridium perfringens:

1200 to 2700 mg/day in 2, 3 or 4 equal doses.

For more serious infections, these doses may have to be increased. In life-threatening situations due to either aerobes or anaerobes, these doses may be increased. Doses of as much as 4800 mg daily have been given intravenously to adults. See Dilution and Infusion Rates section below.

Single I.M. injections of greater than 600 mg are not recommended.

Alternatively, drug may be administered in the form of a single rapid infusion of the first dose followed by continuous I.V. infusion as follows:

To maintain serum
clindamycin levels
Above 4 mcg/mL
Above 5 mcg/mL
Above 6 mcg/mL

Rapid infusion
rate
10 mg/min for 30 min
15 mg/min for 30 min
20 mg/min for 30 min

Maintenance infusion
rate
0.75 mg/min
1 mg/min
1.25 mg/min

Neonates (less than 1 month):

15 to 20 mg/kg/day in three to four equal doses. The lower dosage may be adequate for small prematures.

Pediatric patients (1 month of age to 16 years):

Parenteral (I.M. or I.V.) administration: 20 to 40 mg/kg/day in 3 or 4 equal doses. The higher doses would be used for more severe infections. As an alternative to dosing on a body weight basis, pediatric patients may be dosed on the basis of square meters body surface: 350 mg/m^2/day for serious infections and 450 mg/m^2/day for more severe infections.

Parenteral therapy may be changed to clindamycin palmitate hydrochloride for oral solution or clindamycin hydrochloride capsules when the condition warrants and at the discretion of the physician.

In cases of β-hemolytic streptococcal infections, treatment should be continued for at least 10 days.

Dilution and Infusion Rates:

Clindamycin phosphate must be diluted prior to I.V. administration. The concentration of clindamycin in diluent for infusion should not exceed 18 mg per mL. Infusion rates should not exceed 30 mg per minute. The usual infusion dilutions and rates are as follows:

Dose | Diluent | Time
300 mg 600 mg 900 mg 1200 mg | 50 mL 50 mL 50-100 mL 100 mL | 10 min 20 min 30 min 40 min

Administration of more than 1200 mg in a single 1-hour infusion is not recommended.

Parenteral drug products should be inspected visually for particulate matter and discoloration prior to administration, whenever solution and container permit.

Dilution and Compatibility:

Physical and biological compatibility studies monitored for 24 hours at room temperature have demonstrated no inactivation or incompatibility with the use of clindamycin phosphate in I.V. solutions containing sodium chloride, glucose, calcium or potassium, and solutions containing vitamin B complex in concentrations usually used clinically. No incompatibility has been demonstrated with the antibiotics cephalothin, kanamycin, gentamicin, penicillin or carbenicillin.

The following drugs are physically incompatible with clindamycin phosphate: ampicillin sodium, phenytoin sodium, barbiturates, aminophylline, calcium gluconate, and magnesium sulfate.

The compatibility and duration of stability of drug admixtures will vary depending on concentration and other conditions.

Physico-Chemical Stability of Diluted Solutions of Clindamycin:

Room temperature: 6, 9, and 12 mg/mL (equivalent to clindamycin base) in 5% Dextrose Injection, 0.9% Sodium Chloride Injection, or Lactated Ringer’s Injection in glass bottles or minibags, demonstrated physical and chemical stability for at least 16 days at 25°C. Also, 18 mg/mL (equivalent to clindamycin base) in 5% Dextrose Injection, in minibags, demonstrated physical and chemical stability for at least 16 days at 25°C.

Refrigeration: 6, 9 and 12 mg/mL (equivalent to clindamycin base) in 5% Dextrose Injection, 0.9% Sodium Chloride Injection, or Lactated Ringer’s Injection in glass bottles or minibags, demonstrated physical and chemical stability for at least 32 days at 4°C.

IMPORTANT: This chemical stability information in no way indicates that it would be acceptable practice to use this product well after the preparation time. Good professional practice suggests that compounded admixtures should be administered as soon after preparation as is feasible.

Frozen: 6, 9 and 12 mg/mL (equivalent to clindamycin base) in 5% Dextrose Injection, 0.9% Sodium Chloride Injection, or Lactated Ringer’s Injection in minibags demonstrated physical and chemical stability for at least eight weeks at -10°C.

Frozen solutions should be thawed at room temperature and not refrozen.

Caution: Do not use plastic containers in series connections. Such use could result in air embolism due to residual air being drawn from the primary container before administration of the fluid from the secondary container is complete.

HOW SUPPLIED

Clindamycin Injection, USP (150 mg/mL) is supplied as follows:

List No. | Volume | Type Container | Clindamycin base Total Content
54868-3695-0 | 2 mL | Single-dose fliptop vial/ 25 vials per tray | 300 mg

Store at 20 to 25°C (68 to 77°F). [See USP Controlled Room Temperature.]

Do not refrigerate.

ANIMAL TOXICOLOGY

One year oral toxicity studies in Spartan Sprague− Dawley rats and beagle dogs at dose levels up to 300 mg/kg/day (approximately 1.1 and 3.6 times the highest recommended adult human dose based on mg/m^2, respectively) have shown clindamycin to be well tolerated. No appreciable difference in pathological findings has been observed between groups of animals treated with clindamycin and comparable control groups. Rats receiving clindamycin hydrochloride at 600 mg/kg/day (approximately 2.1 times the highest recommended adult human dose based on mg/m^2) for 6 months tolerated the drug well; however, dogs dosed at this level (approximately 7.2 times the highest recommended adult human dose based on mg/m^2) vomited, would not eat, and lost weight.

Revised: March, 2008

REFERENCES

1. Smith RB, Phillips JP: Evaluation of Clindamycin Hydrochloride and Clindamycin Phosphate in an Aged Population. Upjohn TR:8147-9122-021, December 1982.
2. Bauer AW, Kirby WMM, Sherris JC, Turck M: Antibiotic susceptibility testing by a standardized single disk method, Am J Clin Path, 45:493-496, 1966. Standardized Disk Susceptibility Test, Federal Register 37:20527-29, 1972.
3. National Committee for Clinical Lab. Standards. Methods for Antimicrobial Susceptibility Testing of Anaerobic Bacteria-Second Edition; Tentative Standard. NCCLS publication M11-T2. Villanova, PA; NCCLS; 1988.

Printed in USA

EN-1754

Hospira, Inc., Lake Forest, IL 60045 USA

Relabeling of "Additional Barcode Label" by:
Physicians Total Care, Inc.
Tulsa, OK 74146

PRINCIPAL DISPLAY PANEL

Clindamycin Injection, USP (300 mg/2 mL)